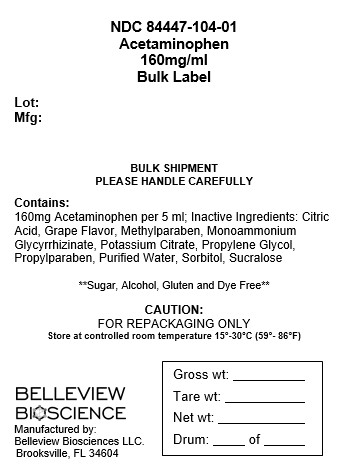 DRUG LABEL: Acetaminophen
NDC: 84447-104 | Form: SOLUTION
Manufacturer: Belleview Biosciences LLC
Category: otc | Type: HUMAN OTC DRUG LABEL
Date: 20241112

ACTIVE INGREDIENTS: ACETAMINOPHEN 160 mg/5 mL
INACTIVE INGREDIENTS: METHYLPARABEN; POTASSIUM CITRATE; PROPYLPARABEN; SORBITOL; PROPYLENE GLYCOL; WATER; SUCRALOSE; AMMONIUM GLYCYRRHIZATE; ANHYDROUS CITRIC ACID

CuraNOL

Directions:

■ Dosage may be repeated every 4 hours, or as directed by doctor

■ Do not exceed recommended dose.

■ Find dose in chart below ■ If possible, use weight to dose, otherwise use age

Dosage
Weight (lbs) | Under 24 | 24-35 | 36-47 | 48-59 | 60-71 | 72-95 | Over 95
Age (years) | Under 2 | 2 to 3 | 4 to5 | 6 to 8 | 9 to 10 | 11 | 12 to Adult
Dosage Teaspoonful (tsp) | consult a doctor | 1 tsp (5 mL) | 1 1/2 tsp (7.5 mL) | 2 tsp (10mL) | 2 1/2 tsp (12.5 mL) | 3 tsp (15 mL) | 4 tsp (20mL)

Warnings:Liver Warning: This product contains acetaminophen.

Severe liver damage may occur if.

■ adults take more than 6 doses in 24 hours, which is the maximum daily amount

■ child takes more than 5 doses in 24 hours, which is the maximum daily amount

■ taken with other drugs containing acetaminophen (prescription or nonprescription)

■ adult has 3 or more alcoholic drinks while using this product.

Allergy Alert: Acetaminophen may cause severe skin reactions. Symptoms may

include: ■ skin reddening ■ blisters ■rash

If skin reaction occurs, stop use and seek medical help right away

Do not use with any other product containing acetaminophen (prescription or

nonprescription), this will provide more than the recommended dose (overdose)

of acetaminophen and could cause serious health concerns. If you are not sure

whether a drug contains acetaminophen, ask a doctor or pharmacist.

WHEN USING THIS PRODUCT, DO NOT EXCEED RECOMMENDED DOSE

Ask a doctor before use if you have a liver disease.

Ask a doctor or pharmacist before use if you are taking the blood thinning drug warfarin.

Stop use and ask doctor if: ■ pain gets worse or lasts more than 10 days in adults

■ pain gets worse or lasts more than 5 days in children under 12 years

fever gets worse or lasts more than 3 days ■ new symptoms occur ■ redness

or swelling is present. These could be signs of a serious condition

If pregnant or breast-feeding, ask a health professional before use.

Inactive ingredients:Citric Acid, Flavor, Methylparaben, Monoammonium

Glycyrrhizinate, Potassium Citrate, Propylene Glycol, Propylparaben, Purified Water, Sorbitol,

Sucralose

INDICATIONS AND USAGE

Uses:Temporarily relieves minor aches and pains due to: ■ headache

■ backache ■ muscular aches ■ minor pain of arthritis ■ the common cold

■ toothache ■ premenstrual and menstrual cramps

Temporarily reduces fever.

Keep out of reach of children.

Purpose:

Pain reliever/Fever reducer

Active Ingredient(in each 5 mL tsp)

Acetaminophen,160mg